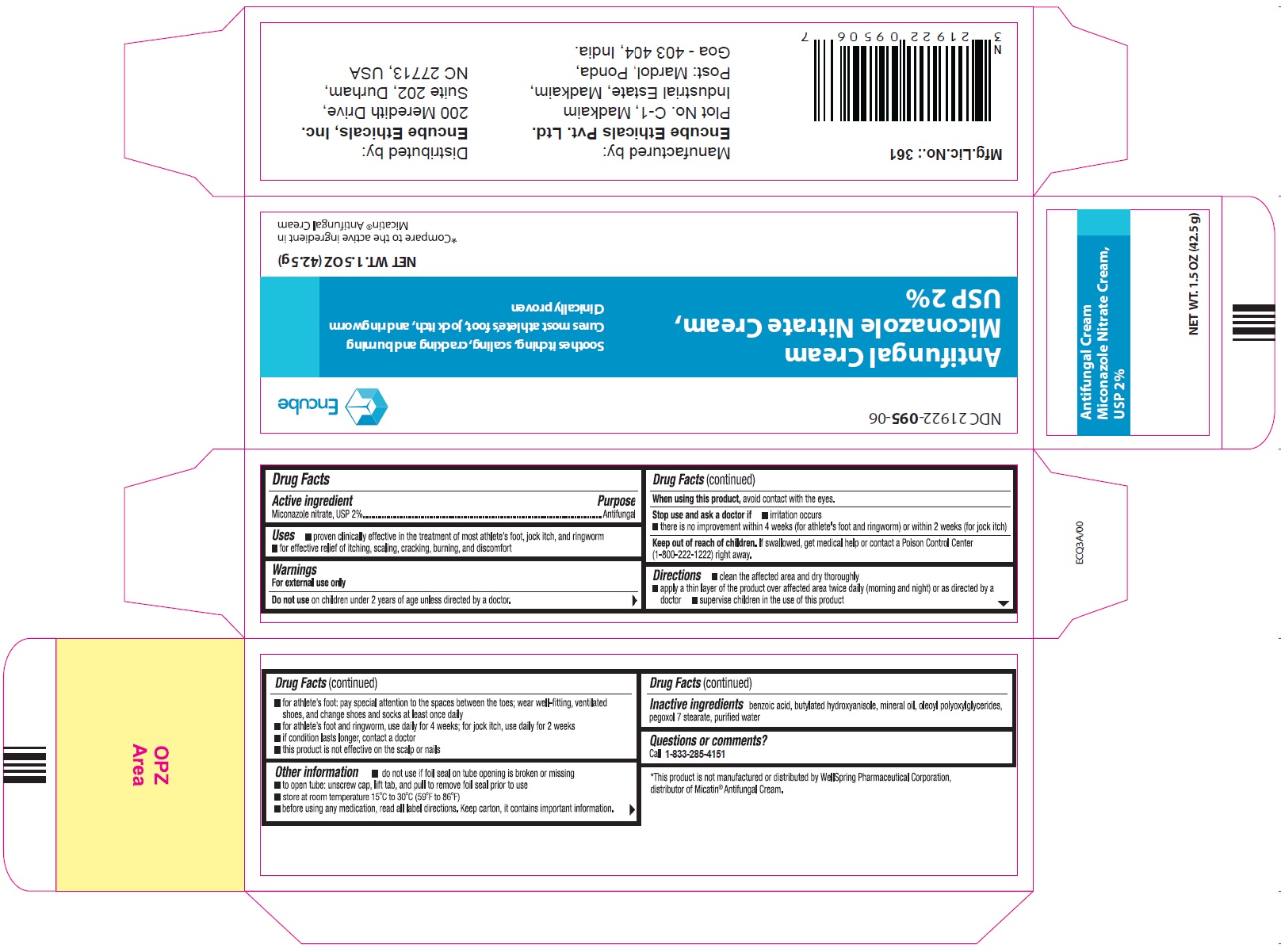 DRUG LABEL: Antifungal Cream
NDC: 21922-095 | Form: CREAM
Manufacturer: Encube Ethicals, Inc.
Category: otc | Type: HUMAN OTC DRUG LABEL
Date: 20250904

ACTIVE INGREDIENTS: MICONAZOLE NITRATE 2 g/100 g
INACTIVE INGREDIENTS: BENZOIC ACID; BUTYLATED HYDROXYANISOLE; MINERAL OIL; APRICOT KERNEL OIL PEG-6 ESTERS; PEGOXOL 7 STEARATE; WATER

Antifungal Cream
Miconazole Nitrate Cream,
USP 2%

ACTIVE INGREDIENT(S)

Miconazole nitrate, USP 2%

PURPOSE

Antifungal

USE(S)

■ proven clinically effective in the treatment of most athlete's foot, jock itch, and ringworm

■ for effective relief of itching, scaling, cracking, burning, and discomfort

WARNINGS

For external use only

DO NOT USE

on children under 2 years of age unless directed by a doctor.

WHEN USING THIS PRODUCT

avoid contact with the eyes.

STOP USE AND ASK DOCTOR IF

■ irritation occurs

■ there is no improvement within 4 weeks (for athlete's foot and ringworm) or within 2 weeks (for jock itch)

KEEP OUT OF REACH OF CHILDREN

If swallowed, get medical help or contact a Poison Control Center (1-800-222-1222) right away.

DIRECTIONS

■ clean the affected area and dry thoroughly

■ apply a thin layer of the product over affected area twice daily (morning and night) or as directed by a doctor

■ supervise children in the use of this product

■ for athlete's foot: pay special attention to the spaces between the toes; wear well-filling, ventilated shoes, and change shoes and socks at least once daily

■ for athlete's foot and ringworm, use daily for 4 weeks; for jock itch, use daily for 2 weeks

■ if condition lasts longer, contact a doctor

■ this product is not effective on the scalp or nails

OTHER INFORMATION

■ do not use if foil seal on tube opening is broken or missing

■ to open tube: unscrew cap, lift tab, and pull to remove foil seal prior to use

■ store at room temperature 15°C to 30°C (59°F to 86°F)

■ before using any medication, read all label directions. Keep carton, it contains important information.

INACTIVE INGREDIENTS

benzoic acid, butylatyIated; hydroxyanisole, mineral oil, oleoyl polyoxylglycerides, pegoxol 7stearate, purified water

QUESTIONS OR COMMENTS?

Call 1-833-285-4151

PRINCIPAL DISPLAY PANEL

Antifungal Cream
Miconazole Nitrate Cream, USP 2%

NET WT. 1.5 OZ (42.5 g)